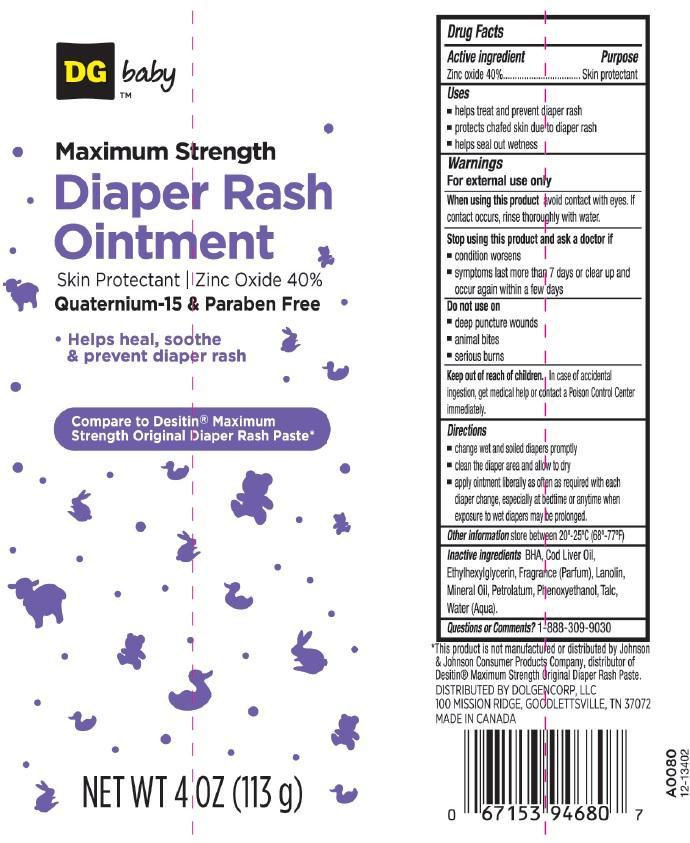 DRUG LABEL: DG BABY DIAPER RASH
NDC: 55910-334 | Form: OINTMENT
Manufacturer: DOLGENCORP INC
Category: otc | Type: HUMAN OTC DRUG LABEL
Date: 20150702

ACTIVE INGREDIENTS: ZINC OXIDE 40 g/100 g
INACTIVE INGREDIENTS: BUTYLATED HYDROXYANISOLE; COD LIVER OIL; ETHYLHEXYLGLYCERIN; LANOLIN OIL; MINERAL OIL; PETROLATUM; PHENOXYETHANOL; TALC; WATER

DRUG FACTS

ACTIVE INGREDIENT

ZINC OXIDE 40%

PURPOSE

SKIN PROTECTANT

USES

- HELPS TREAT AND PREVENT DIAPER RASH
- PROTECTS CHAFED SKIN DUE TO DIAPER RASH
- HELPS SEAL OUT WETNESS

WARNINGS

FOR EXTERNAL USE ONLY

WHEN USING THIS PRODUCT

AVOID CONTACT WITH EYES. IF CONTACT OCCURS, RINSE THOROUGHLY WITH WATER

STOP USING THIS PRODUCT AND ASK A DOCTOR IF

- CONDITION WORSENS
- SYMPTOMS LAST MORE THAN 7 DAYS OR CLEAR UP AND OCCUR AGAIN WITHIN A FEW DAYS

DO NOT USE ON

- DEEP PUNCTURE WOUNDS
- ANIMAL BITES
- SERIOUS BURNS

KEEP OUT OF REACH OF CHILDREN

IN CASE OF ACCIDENTAL INGESTION, GET MEDICAL HELP OR CONTACT A POISON CONTROL CENTER IMMEDIATELY

DIRECTIONS

- CHANGE WET AND SOILED DIAPERS PROMPTLY
- CLEAN THE DIAPER AREA AND ALLOW TO DRY
- APPLY OINTMENT LIBERALLY AS OFTEN AS REQUIRED WITH EACH DIAPER CHANGE, ESPECIALLY AT BEDTIME OR ANYTIME WHEN EXPOSURE TO WET DIAPERS MAY BE PROLONGED.

OTHER INFORMATION

STORE BETWEEN 20°-25°C (68°-77°F)

INACTIVE INGREDIENTS

BHA, COD LIVER OIL, ETHYLHEXYLGLYCERIN, FRAGRANCE (PARFUM), LANOLIN, MINERAL OIL, PETROLATUM, PHENOXYETHANOL, TALC, WATER (AQUA)

QUESTIONS OR COMMENTS?

1-888-309-9030